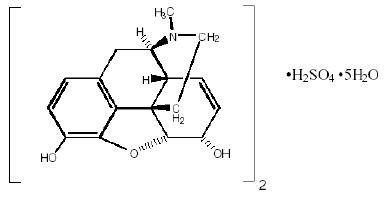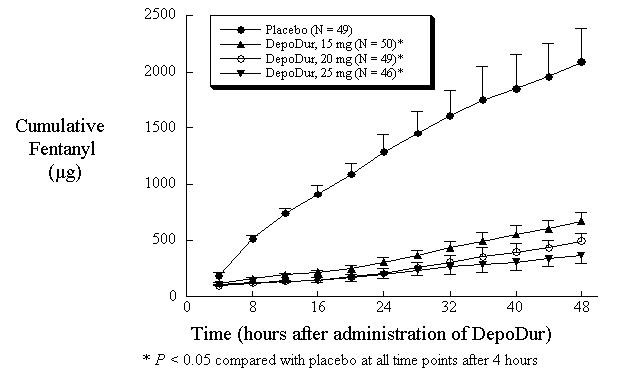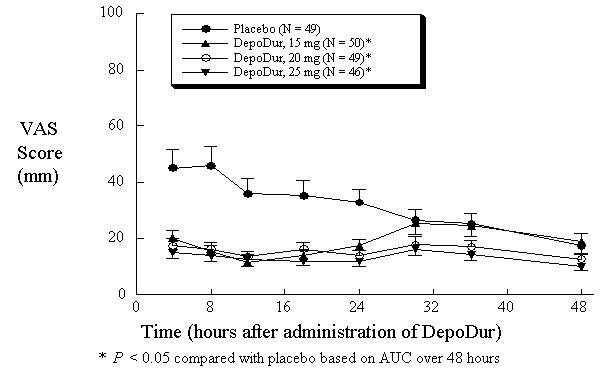 DRUG LABEL: Unknown
Manufacturer: Pacira Pharmaceuticals Inc.
Category: prescription | Type: HUMAN PRESCRIPTION DRUG LABELING
Date: 20080110
DEA Schedule: CII

DepoDur®
(morphine sulfate extended-release liposome injection)
CII
Rx Only

DESCRIPTION

DepoDur (morphine sulfate extended-release liposome injection) is a sterile suspension of multivesicular liposomes using proprietary DepoFoam® formulation technology containing morphine sulfate, intended for epidural administration.

Chemically, morphine sulfate is 7, 8-didehydro-4, 5α-epoxy-17-methylmorphinan-3, 6α -diol sulfate (2:1) (salt) pentahydrate with a molecular weight of 758. Morphine sulfate pentahydrate has the following structural formula:

Morphine base has a pKa of 7.9, with an octanol/water partition coefficient of 1.42 at physiologic pH 7.4. At this pH, morphine’s tertiary amino group is mostly ionized, making the molecule water-soluble.

DepoDur is a sterile, non-pyrogenic, white to off-white, preservative-free suspension of multivesicular lipid-based particles containing Morphine Sulfate, USP. The median diameter of the liposome particles is in the range of 17 to 23 μm. The liposomes are suspended in a 0.9% sodium chloride solution. Each vial contains morphine sulfate (expressed as the pentahydrate) at a nominal concentration of 10 mg/mL. Inactive ingredients and their approximate concentrations are: 1,2-dioleoyl-sn-glycero-3‑phosphocholine (DOPC), 4.2 mg/mL; cholesterol, 3.3 mg/mL; 1,2-dipalmitoyl-sn-glycero-3‑phospho-rac-(1-glycerol) (DPPG), 0.9 mg/mL; tricaprylin, 0.3 mg/mL; and triolein, 0.1 mg/mL. The pH of DepoDur is in the range of 5.0 to 8.0.

After the administration of DepoDur into the epidural space, morphine sulfate is released from the multivesicular liposomes over a period of time.

Liposomal encapsulation or incorporation in a lipid complex can substantially affect a drug’s functional properties relative to those of the unencapsulated or nonlipid-associated drug. In addition, different liposomal or lipid-complexed products with a common active ingredient may vary from one another in the chemical composition and physical form of the lipid component. Such differences may affect functional properties of these drug products. DO NOT SUBSTITUTE.

CLINICAL PHARMACOLOGY

Mechanism of Action

Epidural administration of morphine sulfate results in analgesia without attendant loss of motor, sensory, or sympathetic function.

Morphine released from DepoDur is absorbed both neuraxially and systemically.

Morphine, a pure opiate agonist, is relatively selective for the μ-receptor, although it can interact with other opiate receptors at higher doses. In addition to analgesia, the widely diverse effects of morphine include respiratory depression, drowsiness, changes in mood, decreased gastrointestinal motility, nausea, vomiting, and alterations of the endocrine and autonomic nervous system.

Pharmacodynamics

The effects described below are common to all morphine-containing products.

Effects on the Central Nervous System (CNS): The principal therapeutic action of morphine is analgesia. Other therapeutic effects of morphine include anxiolysis, euphoria and feelings of relaxation. Although the precise mechanism of the analgesic action is unknown, specific CNS opiate receptors and endogenous compounds with morphine-like activity have been identified throughout the brain and spinal cord and are likely to play a role in the expression and perception of analgesic effects. As with all drugs in the opiate class, morphine can cause respiratory depression, in part by a direct effect on the brainstem respiratory centers. Morphine and related opiates depress the cough reflex by direct effect on the cough center in the medulla. Antitussive effects may occur with doses lower than those usually required for analgesia. Morphine may cause miosis, even in total darkness. Pinpoint pupils are a sign of opiate overdose; however, when asphyxia is present during opiate overdose, marked mydriasis occurs.

Effects on the Gastrointestinal Tract and on Other Smooth Muscle: Gastric, biliary and pancreatic secretions are decreased by morphine. Morphine causes a reduction in motility and is associated with an increase in tone in the antrum of the stomach and duodenum. Digestion of food in the small intestine is delayed and propulsive contractions are decreased. Propulsive peristaltic waves in the colon are decreased, while tone can be increased to the point of spasm, often resulting in constipation. Morphine can cause a marked increase in biliary tract pressure as a result of spasm of the sphincter of Oddi. Morphine may also cause spasm of the sphincter of the urinary bladder.

Effects on the Cardiovascular System: In therapeutic doses, morphine does not usually exert major effects on the cardiovascular system. Morphine, like other opiates, produces peripheral vasodilatation that may result in orthostatic hypotension and fainting. Release of histamine can occur, which may play a role in opiate-induced hypotension. Manifestations of histamine release and/or peripheral vasodilatation may include pruritus, flushing, red eyes and sweating.

Pharmacokinetics

Epidural administration of DepoDur results in both systemic absorption of morphine sulfate and absorption of morphine sulfate through the meninges into the intrathecal space. The relative absorption systemically versus intrathecally is unknown for DepoDur.

Absorption

Relative systemic bioavailability of DepoDur compared to epidurally administered morphine injection was determined in 19 patients (Table 1).

Table 1: Pharmacokinetics of DepoDur and Morphine Sulfate Injection (Mean ± SD)
 | DepoDur 5 mg; (n = 10) |  | Morphine Sulfate Injection; 5 mg; (n = 9)
Parameter | Mean | SD | Mean | SD
Cmax (ng/mL) | 7.1 | 3.4 | 23.8 | 12.8
tmax (hr)* | 1.0 | (0.3–4.0) | 0.3 | (0.3–2.0)
AUC (ng•hr/mL) | 38.8 | 10.4 | 42.8 | 8.4
t1/2 (hr) | 3.8 | 1.0 | 2.2 | 0.5
*Median (range)

DepoDur systemic AUC was comparable to that of morphine sulfate injection (approximately 90%), however, systemic Cmax was 30 % of that of morphine sulfate injection.

Based on systemic AUC, DepoDur appears to exhibit dose proportionality over a dose range of 5 to 25 mg. In contrast, systemic Cmax did not exhibit dose-proportionality and tended to increase by an amount less than the proportional change in dose (Table 2).

Table 2: Morphine Plasma Pharmacokinetic Parameters (Mean, SD) Following Epidural Administration of DepoDur
Parameter | DepoDur 5 mg (n=14) | DepoDur 10 mg (n=36) | DepoDur 15 mg (n=71) | DepoDur 20 mg (n=63) | DepoDur 25 mg (n=32) | DepoDur 30 mg (n=25)
Cmax (ng/mL) | 9.4 (5.7) | 20.0 (9.5) | 18.6 (10.4) | 26.4 (18.6) | 22.6 (15.4) | 47.3 (28.9)
AUC0–∞ (ng•hr/mL) | 41.0 (10.6) | 124.9 (98.1) | 131.6 (73.7) | 185.9 (81.4) | 207.3 (77.7) | 341.5 (136.9)
t1/2 (hr) | 4.2 (2.1) | 16.2 (19.7) | 20.0 (20.6) | 23.9 (25.4) | 32.9 (24.2) | 25.6 (14.6)

Distribution

After morphine sulfate has been released from DepoDur and is absorbed systemically, morphine distribution is expected to be the same as for other morphine formulations.

Once absorbed, morphine is distributed to skeletal muscle, kidneys, liver, intestinal tract, lungs, spleen and brain. The volume of distribution of morphine is approximately 1 to 4 L/kg. Morphine is 20 to 35% reversibly bound to plasma proteins. Morphine also crosses the placental membranes and has been found in breast milk.

Metabolism

After morphine sulfate has been released from DepoDur and is absorbed systemically, morphine metabolism is expected to be the same as for other morphine formulations.

The major pathway of the detoxification of morphine is conjugation, either with D‑glucuronic acid in the liver to produce glucuronides or with sulfuric acid to give morphine-3-etheral sulfate. Although a small fraction (less than 5%) of morphine is demethylated, for all practical purposes, virtually all morphine is converted to glucuronide metabolites including morphine-3-glucuronide, M3G (about 50%) and morphine-6-glucuronide, M6G (about 5 to 15%). M3G has no significant analgesic activity. M6G has been shown to have opiate agonist and analgesic activity in humans.

Excretion

After morphine sulfate has been released from DepoDur and is absorbed systemically, morphine excretion is expected to be the same as for other morphine formulations. DepoDur is intended for single dose administration, therefore, accumulation of morphine or its metabolites is not expected even in patients with impaired hepatic or renal function.

Approximately 10% of morphine dose is excreted unchanged in the urine. Most of the dose is excreted in the urine as M3G and M6G. A small amount of the glucuronide metabolites is excreted in the bile and there is some minor enterohepatic cycling. Seven to 10% of administered morphine is excreted in the feces. The mean adult plasma clearance is about 20–30 mL/minute/kg. The effective terminal half-life of morphine after IV administration is reported to be approximately 2 hours. In some studies involving longer periods of plasma sampling, a longer terminal half-life of morphine of about 15 hours was reported.

Special Populations

Geriatric: Elderly patients (aged 65 years or older) may have increased sensitivity to DepoDur, as with other opiates. In elderly patients (over 65 years of age), the Cmax was similar to that of patients 65 years of age or younger, but the clearance in elderly patients was reduced by approximately 13%.

Pediatric: The pharmacokinetics of DepoDur have not been studied in pediatric patients.

Hepatic Failure: Systemic morphine pharmacokinetics have been reported to be significantly altered in patients with cirrhosis. Clearance was found to decrease with a corresponding increase in half-life. The M3G and M6G to morphine plasma AUC ratios also decreased in these subjects, indicating diminished metabolic activity. DepoDur is intended for single-dose administration, therefore accumulation of morphine or its metabolites is not expected even in patients with impaired hepatic function.

Renal Insufficiency: Systemic morphine pharmacokinetics are altered in patients with renal failure. Clearance is decreased and the metabolites, M3G and M6G, may accumulate to much higher plasma levels in patients with renal failure as compared to patients with normal renal function. DepoDur is intended for single-dose administration, therefore accumulation of morphine or its metabolites is not expected even in patients with impaired renal function.

Drug-Drug Interactions: Other than the interactions with a lidocaine with epinephrine test dose (see below), no other pharmacokinetic drug-drug interactions have been examined in vivo. In-vitro studies suggest a similar interaction is anticipated with other amide local anesthetics. No in-vitro or in-vivo studies have been performed with ester local anesthetics. Known drug-drug interactions involving morphine are pharmacodynamic, not pharmacokinetic (see PRECAUTIONS, Drug Interactions).

Test Dose Interaction

Epidural administration of a 3-mL test dose (lidocaine 1.5% and epinephrine 1:200,000) may affect the release of morphine sulfate from DepoDur (see PRECAUTIONS, Drug Interactions). This issue has been examined in patients who received epidural administration of 15 mg of DepoDur at various time intervals after the test dose (Table 3). The test groups included a no-test-dose group and 3-, 10- and 15-minute delays between test dose and DepoDur administration. Additionally, saline flush after the test dose was assessed. The serum concentration of morphine was measured as a biomarker.

Table 3: Impact of Test Dose Administration on Peak Serum Concentration of DepoDur
Minutes Between Test Dose and DepoDur Administration | N | Mean tmax; hr (SD) | Mean Cmax; ng/mL (SD) | Median Cmax; ng/mL | Min–Max; ng/mL
No test dose | 6 | 2.5 (2.1) | 11.5 (7.4) | 10.2 | 4.1–23.5
Flush + 3 | 8 | 0.2 (0.04) | 30.2 (8.5) | 31.4 | 15.8–40.1
Flush + 10 | 7 | 0.6 (0.7) | 15.6 (9.3) | 13.3 | 7.4–34.0
Flush + 15 | 8 | 0.5 (0.3) | 11.4 (6.4) | 11.4 | 2.0–20.0
No Flush + 3 | 8 | 0.4 (0.7) | 25.6 (10.1) | 22.6 | 15.2–45.4

Serum morphine Cmax was comparable to that of the no-test-dose group if DepoDur was administered 15 minutes after the test dose.
Anesthetics other than lidocaine with epinephrine have not been evaluated.

Clinical Studies

The efficacy of DepoDur was demonstrated in four clinical trials comprised of 876 patients undergoing surgical procedures such as hip arthroplasty, prostatectomy, colon resection and cesarean section. In these clinical trials, efficacy was assessed for at least 48 hours and safety for up to 30 days after DepoDur administration.

Hip Arthroplasty

Two randomized, double-blind, placebo-controlled, parallel-group, dose-ranging studies evaluated the safety and efficacy of 10, 15, 20, 25, and 30 mg DepoDur in 314 patients undergoing hip arthroplasty. The mean age of patients was 59 years (range 18 to 88 years). Study medication was administered approximately 30 minutes before surgery. Post-operatively, patients self-administered intravenous fentanyl via patient-controlled analgesia (PCA) to maintain satisfactory analgesia.

In one study (N=194), single epidural administration of 15, 20, and 25 mg DepoDur provided superior analgesic efficacy compared to placebo (epidural saline injection followed by IV fentanyl PCA), as measured by decreased fentanyl use (Figure 1) and Visual Analog Scores (VAS) (Figure 2). The second clinical study in hip arthroplasty revealed similar results.

Figure 1: Cumulative Fentanyl Usage Over 48 Hours (Mean, SE)

Figure 2:Pain Intensity Scores Over 48 hours (Mean, SE)

Lower Abdominal Surgery

A randomized, double-blind, parallel-group study evaluated the safety and efficacy of single epidural doses of 10, 15, 20, and 25 mg DepoDur compared to 5 mg DepoDur or 5 mg morphine sulfate in 487 patients undergoing lower abdominal surgery (i.e. surgery via an abdominal incision below umbilicus). Study medication was administered approximately 30 minutes prior to surgery. Post-operatively, patients self-administered intravenous fentanyl via patient-controlled analgesia (PCA) to maintain satisfactory analgesia. A dose response was observed, demonstrating a reduction in IV fentanyl use over the 48-hour period.

Cesarean Section

A randomized, double-blind, parallel-group study evaluated the safety and efficacy of single epidural doses of 5, 10, and 15 mg DepoDur compared to epidural morphine sulfate injection (5 mg) in 75 patients undergoing elective cesarean section under intrathecal anesthesia. Study medication was administered following delivery and clamping of the umbilical cord. At the investigator’s discretion, patients were permitted to receive acetaminophen with codeine or intravenous morphine sulfate as an intermittent bolus or via PCA pump, post-operatively. DepoDur doses of 10 and 15 mg resulted in reduced use of rescue medication and improved post-operative analgesia based on AUC analysis of VAS pain scores at rest (R) and with activity (A), compared to morphine sulfate on average over the 48-hour period following elective cesarean section (Table 4).

Table 4: Cesarean Section: Total Opiate Use, Pain VAS at Rest and with Activity
Efficacy Parameters | Morphine Sulfate Injection | DepoDur
 | 5 mg | 10 mg | 15 mg
Opiate use (mg, morphine equivalents*) 0–48 h, median† | 38.2 | 19.0 | 18.0
Opiate use (mg, morphine equivalents*) 24–48 h, median§ | 16.3 | 9.0 | 6.0
VAS-R AUC 0–48 h, mean ± SD† | 1186 ± 939 | 454 ± 334 | 484 ± 425
VAS-A AUC 0–48 h, mean ± SD† | 2086 ± 875 | 1235 ± 775 | 1036 ± 726
*Median;†p< 0.05; § p< 0.001

INDICATIONS AND USAGE

DepoDur is an extended-release liposome injection of morphine sulfate intended for single-dose administration by the epidural route, at the lumbar level, for the treatment of pain following major surgery. DepoDur is administered prior to surgery or after clamping the umbilical cord during cesarean section.

DepoDur is not intended for intrathecal, intravenous, or intramuscular administration. Administration of DepoDur into the thoracic epidural space or higher has not been evaluated and therefore is not recommended.

CONTRAINDICATIONS

DepoDur is contraindicated in patients with known hypersensitivity to morphine, morphine salts, or any components of the product. DepoDur, as with all opiates, is contraindicated in patients with respiratory depression, acute or severe bronchial asthma, and upper airway obstruction. Any contraindications for an epidural injection preclude the administration of DepoDur. DepoDur, as with all opiates, is contraindicated in any patient who has or is suspected of having paralytic ileus. DepoDur should not be used in patients with suspected or known head injury or increased intracranial pressure.

DepoDur is an opiate analgesic which causes vasodilatation that may exacerbate hypotension and hypoperfusion and, therefore, is contraindicated in circulatory shock.

WARNINGS

Due to the risk of severe adverse events when the epidural route of administration is employed, patients must be observed in a fully equipped and staffed environment for at least 48 hours after administration. The facility must be equipped to resuscitate patients with severe opiate overdosage, and the personnel must be familiar with the use and limitations of specific narcotic antagonists (naloxone, naltrexone) in such cases.

No clinical studies have evaluated the safety of administration of DepoDur into the intrathecal space. DepoDur is intended for administration by the epidural route only. However, cases of intrathecal administration of DepoDur have been reported during post-marketing experience. In all cases, signs of prolonged respiratory depression were observed requiring narcotic antagonist (naloxone) administration or ventilatory support.

Prolonged and serious respiratory depression or apnea has occurred when administration of epidural DepoDur was associated with subarachnoid puncture. In these cases, respiratory depression has occurred within 12 hours of DepoDur administration following apparent recovery from anesthesia. Respiratory depression resulting from DepoDur can be treated successfully with a naloxone bolus or, more commonly, a naloxone infusion; intubation and mechanical ventilation may be necessary in some cases.

Because intrathecal leakage from the epidural space may occur through a breached dural membrane, especially when the epidural drug is administered in a bolus, DepoDur should not be administered to a patient following a recent dural puncture without vigilant monitoring of respiratory function for a prolonged period (48 hours) with provision for emergency mechanical ventilation to minimize the risk of serious respiratory depression.

DepoDur should be administered by or under the direction of a physician experienced in the techniques associated with epidural drug administration and familiar with patient management following epidural opiate administration, including the management of respiratory depression.

Prior to drug administration, the physician should be familiar with patient conditions (such as infection at the injection site, bleeding diathesis, current and anticipated anticoagulant therapy, etc.) that call for special evaluation of the benefit versus risk potential.

Impaired Respiration

Respiratory depression is the chief hazard of all opiate preparations. Respiratory depression occurs more frequently in elderly or debilitated patients and in those suffering from conditions accompanied by hypoxia or hypercapnia in whom even moderate therapeutic doses may significantly decrease pulmonary ventilation.

Administration of opiates with or without coadministration of other sedative or hypnotic drugs can worsen airway obstruction in patients with obstructive sleep-apnea syndrome. Patients who are obese are at particular risk for this syndrome, which may be undiagnosed prior to administration.

Respiratory depression can occur with DepoDur. Four percent of the patients who received DepoDur required treatment with narcotic antagonists for respiratory depression. Ninety percent of events of respiratory depression started within the first 24 hours after dosing with DepoDur. However, the incidence of respiratory depression starting after 48 hours, potentially related to DepoDur, was 0.6% (5 of 900 patients). Patients at increased risk of respiratory depression such as those with impaired respiratory drive, sleep apnea, concomitant sedation or the elderly, may require monitoring for periods longer than 48 hours.

Because of the risk of respiratory depression, the facility must be equipped to resuscitate patients. Patients must be closely monitored in a fully equipped and staffed environment for a minimum of 48 hours.

If the surgical procedure is cancelled after the administration of DepoDur, the risk of respiratory depression may be increased, and patients should be monitored with a high level of vigilance.

Epidural local anesthetics should not be used before or after DepoDur, except in the form of a test dose. (See PRECAUTIONS – Drug Interactions) Do not mix or co-administer DepoDur with any other medications including local anesthetics. Once DepoDur has been administered, no other medication should be administered into the epidural space for at least 48 hours.

Misuse, Abuse and Diversion of Opiates

The active ingredient of DepoDur is morphine, a μ-opiate agonist. DepoDur is a Schedule II controlled substance. Such drugs are sought by drug abusers and people with addiction disorders. Diversion of Schedule II products is an act subject to criminal penalty. DepoDur can be abused in a manner similar to other opiate agonists, legal or illicit.

Concerns about abuse, addiction, and diversion should not prevent the proper management of pain. Healthcare professionals should contact their State Professional Licensing Board, or State Controlled Substances Authority for information on how to prevent and detect abuse or diversion of this product.

Hypotensive Effect

DepoDur, like all other opiates, may cause severe hypotension in an individual whose ability to maintain blood pressure has already been compromised by a depleted blood volume or concurrent administration of drugs such as phenothiazines or general anesthetics (see also PRECAUTIONS – Drug Interactions). DepoDur may produce orthostatic hypotension and syncope in ambulatory patients.

In a patient who progresses to circulatory shock, DepoDur may make resuscitation more difficult due to vasodilatation.

Gastrointestinal Obstruction

DepoDur should not be administered to patients with gastrointestinal obstruction, especially paralytic ileus, because DepoDur diminishes propulsive peristaltic waves in the gastrointestinal tract and may prolong the obstruction.

Use with Other Central Nervous System Depressants

The central nervous depressant effects of morphine are potentiated by the presence of other CNS depressants such as alcohol, other opiates, sedatives, antihistaminics or psychotropic drugs. Use of neuroleptics or general anesthetics in conjunction with epidural morphine may increase the risk of respiratory depression.

Labor and Delivery

DepoDur should not be administered to women for vaginal labor and delivery. DepoDur has only been administered to women undergoing cesarean section following clamping of the umbilical cord.

PRECAUTIONS

General

Epidural delivery of opiates is accompanied by risk to the patients and requires a high level of skill to be successfully accomplished. The task of treating these patients must be undertaken by experienced clinical teams, well-versed in patient selection and emerging standards of care. It is critical to adjust the dose of DepoDur for each individual patient, taking into account the patient’s prior experience with opiate analgesics (see DOSAGE AND ADMINISTRATION).

Seizures may result from high doses of morphine. Patients with known seizure disorders should be carefully observed for evidence of morphine-induced seizure activity.

Use in Hepatic or Renal Disease

After morphine sulfate has been released from DepoDur and is absorbed systemically, its distribution, metabolism and excretion are expected to be the same as other morphine formulations. DepoDur is intended for single-dose administration; therefore accumulation of morphine or its metabolites is not expected even in patients with impaired hepatic or renal function.

Use in Biliary Surgery or Disorders of the Biliary Tract

Morphine is released into the systemic circulation after epidural administration. Therefore, smooth muscle hypertonicity may result in biliary colic.

DepoDur should be used with caution in patients with biliary tract disease, including acute pancreatitis, as morphine may cause spasm of the sphincter of Oddi and diminish biliary and pancreatic secretions.

Use with Disorders of the Urinary System

The use of epidural opiate analgesia has been associated with disturbances of micturition, especially in males with prostatic hypertrophy. Early recognition of urinary retention and prompt intervention is indicated.

Post-Surgical Ambulation

Patients with reduced circulating blood volume, impaired myocardial function or those receiving sympatholytic drugs should be monitored for the possible occurrence of orthostatic hypotension, a frequent complication in single-dose epidurally administered morphine analgesia.

Intravenous or Intramuscular Administration

Administration of DepoDur via the intravenous or intramuscular routes has not been studied in humans and DepoDur should not be administered by these routes.

Drug Interactions

Local Anesthetics: Administration of DepoDur three minutes after a 3-mL test-dose (lidocaine 1.5% and epinephrine 1:200,000) increases peak serum concentrations of morphine (SeeCLINICAL PHARMACOLOGY). Increasing the interval between the test dose and DepoDur administration to at least 15 minutes minimizes this pharmacokinetic interaction.

Safety and efficacy of DepoDur when used in conjunction with therapeutic epidural doses of lidocaine with epinephrine (for conduction anesthesia) have not been studied in clinical trials.

CNS Depressants: The concurrent use of other central nervous system (CNS) depressants including sedatives, hypnotics, general anesthetics, droperidol, phenothiazines or other tranquilizers, or alcohol increases the risk of respiratory depression, hypotension, profound sedation, or coma. Use with caution and with vigilant monitoring in patients taking these agents.

Monoamine Oxidase Inhibitors (MAOIs): MAOIs markedly potentiate the action of morphine. DepoDur should not be used in patients taking MAOIs or within 14 days of stopping such treatment.

Muscle Relaxants: Respiratory depression associated with morphine may delay recovery of spontaneous pulmonary ventilation when neuromuscular blocking agents are coadministered.

Carcinogenicity/Mutagenicity/Impairment of Fertility

Studies in animals to evaluate the carcinogenic potential of morphine sulfate have not been conducted. No formal studies to assess the mutagenic potential of morphine have been conducted. In the published literature, the results of in-vitro studies showed that morphine is non-mutagenic in the Drosophila melanogaster lethal mutation assay and produced no evidence of chromosomal aberrations when incubated with murine splenocytes. Contrary to these results, morphine was found to increase DNA fragmentation when incubated in vitro with a human lymphoma cell line. In vivo, morphine has been reported to produce an increase in the frequency of micronuclei in bone marrow cells and immature red blood cells in the mouse micronucleus test and to induce chromosomal aberrations in murine lymphocytes and spermatids. Some of the in‑vivo clastogenic effects reported with morphine in mice may be directly related to increases in glucocorticoid levels produced by morphine in this species.

Pregnancy

Teratogenic Effects (Pregnancy Category C)

No formal studies to assess the teratogenic effects of morphine in animals have been performed. Several literature reports indicate that morphine administered subcutaneously during the early gestational period in mice and hamsters produced neurological, soft tissue and skeletal abnormalities. With one exception, the effects that have been reported were following doses that were maternally toxic and the abnormalities noted were characteristic of those observed when maternal toxicity is present. In one study, following subcutaneous infusion of doses greater than or equal to 0.15 mg/kg in mice, exencephaly, hydronephrosis, intestinal hemorrhage, split supraoccipital, malformed sternebrae, and malformed xiphoid were noted in the absence of maternal toxicity. In the hamster, morphine sulfate given subcutaneously on gestation day eight produced exencephaly and cranioschisis. Morphine was not a significant teratogen in the rat at exposure levels significantly beyond that normally encountered in clinical practice. In one study, however, decreased litter size and viability were observed in the offspring of male rats administered morphine at doses approximately 3-fold the maximum recommended human daily dose (MRHDD) for 10 days prior to mating. In two studies performed in the rabbit, no evidence of teratogenicity was reported at subcutaneous doses up to 100 mg/kg.

In humans, the frequency of congenital anomalies has been reported to be no greater than expected among the children of 70 women who were treated with morphine during the first four months of pregnancy or in 448 women treated with this drug anytime during pregnancy. Furthermore, no malformations were observed in the infant of a woman who attempted suicide by taking an overdose of morphine and other medication during the first trimester of pregnancy.

Nonteratogenic Effects

Published literature indicates that exposure to morphine during pregnancy is associated with reduction in growth and a host of behavioral abnormalities in the offspring of animals. Morphine treatment during gestational periods of organogenesis in rats, hamsters, guinea pigs and rabbits resulted in the following treatment-related embryotoxicity and neonatal toxicity in one or more studies: decreased litter size, embryo-fetal viability, fetal and neonatal body weights, absolute brain and cerebellar weights, lengths or widths at birth and during the neonatal period, delayed motor and sexual maturation, and increased neonatal mortality, cyanosis and hypothermia. Decreased fertility in female offspring, and decreased plasma and testicular levels of luteinizing hormone and testosterone, decreased testes weights, seminiferous tubule shrinkage, germinal cell aplasia, and decreased spermatogenesis in male offspring were also observed. Behavioral abnormalities resulting from chronic morphine exposure of fetal animals included altered reflex and motor skill development, mild withdrawal, and altered responsiveness to morphine persisting into adulthood.

Morphine sulfate should be used by a pregnant woman only if the need for opiate analgesia clearly outweighs the potential risks to the fetus.

Labor and Delivery

See WARNINGS.

Nursing Mothers

In studies of epidural administration of morphine sulfate injection, small amounts of morphine were detected in breast milk. The degree to which morphine sulfate is excreted in human milk following administration of DepoDur has not been studied. Because many drugs are excreted in human milk and because of the potential for adverse reactions in nursing infants from morphine, a decision should be made whether or not to allow nursing during the first 48 hours following DepoDur administration.

Pediatric Use

The safety and effectiveness of DepoDur in pediatric patients below the age of 18 years have not been established and use in this population is not recommended.

Use in the Elderly

DepoDur was studied in clinical trials of 876 subjects; 222 were 65 years of age and older, and 43 of these patients were 75 years of age and over. The efficacy and opiate adverse event profiles in these elderly patients, at the same or lower dose of DepoDur, were similar to those in younger adults (see DOSAGE AND ADMINISTRATION). However, elderly patients (65 years of age or older) may have increased sensitivity to morphine. Comorbid conditions may predispose the elderly population to serious adverse events such as respiratory depression, ileus, hypotension and myocardial infarction.

In general, caution should be exercised in the selection of the dose of DepoDur for an elderly patient. Dosing normally should be at the low end of the range.

DepoDur should be administered to elderly patients (>65 years) after careful evaluation of their underlying medical condition and consideration of the risks associated with DepoDur. Provision for vigilant perioperative monitoring should be arranged for elderly patients receiving DepoDur.

ADVERSE EVENTS

In controlled and open label clinical studies with DepoDur, the majority of the adverse events were typical of opiate medications and would be expected in the surgical populations studied. The most common adverse events (greater than 10%) reported at least once during therapy in patients treated with DepoDur were decreased oxygen saturation, hypotension, urinary retention, vomiting, constipation, nausea, pruritus, pyrexia, anemia, headache, and dizziness. Adverse events occurring in 5–10% of study patients were hypoxia, tachycardia, insomnia, and flatulence. Other less common side effects (seen in 2–5% of patients receiving DepoDur) included respiratory depression, hypercapnia, paralytic ileus, somnolence, bladder spasm, abdominal distension, hypoesthesia, hypertension, oliguria, bradycardia, anxiety, back pain, increased sweating, dyspepsia, rigors, dyspnea, hypokalemia, paresthesia, and decreased hematocrit.

Of the patients treated with DepoDur in clinical trials, 4% exhibited signs of respiratory depression requiring treatment with narcotic antagonists. In clinical trials, 90% of respiratory depression occurred within 24 hours after administration of DepoDur. However, onset of respiratory depression occurred in 0.6% of patients after more than 48 hours.

During post-marketing experience, central nervous system (CNS) depression, including obtunded feeling, non-arousable condition, unresponsiveness, confusion, and lethargy, has been reported following epidural administration of DepoDur. In most of these cases with CNS depression, there was concomitant administration of different narcotics or hypnotic/sedative medications in the post-operative period.

During post-marketing experience, severe respiratory depression, involving apnea or respiratory arrest, and cardiac arrest have been reported following administration of labeled doses of DepoDur.

Prolonged respiratory depression or apnea may occur when administration of epidural DepoDur is associated with subarachnoid puncture.

DRUG ABUSE AND DEPENDENCE

DepoDur is a μ-agonist opiate and is a Schedule II controlled substance. Morphine, as with other opiates used in analgesia, can be abused and is subject to criminal diversion. Drug addiction is characterized by compulsive use, use for non-medical purposes, and continued use despite harm or risk of harm.

As with all potent μ-agonist opiates, tolerance as well as psychological and physical dependence to morphine may develop irrespective of the route of administration (intravenous, intramuscular, intrathecal, epidural or oral). Tolerance is a condition in which previous exposure to an opiate results in the necessity for increasingly larger doses of the drug in order to produce the same degree of analgesia. Withdrawal symptoms, indicating the presence of psychophysiological dependence, may occur when morphine is discontinued abruptly after chronic administration for analgesia, or upon administration of a drug with full or partial opiate antagonist effects. Care must be taken to avert withdrawal in patients who have been maintained on parenteral/oral opiates prior to epidural administration of DepoDur.

Individuals with a history of opiate or other substance abuse would be considered to be at greater risk of addiction or abuse, given that they are more apt to respond to the euphorigenic and reinforcing properties of morphine. However, concerns about abuse, addiction or diversion of opiates should not prevent proper management of pain.

DepoDur is intended for epidural use only. Abuse of DepoDur may pose a hazard of overdose and death when administered through other routes. This risk is increased with concurrent use of other medications or illicit drugs.

OVERDOSAGE

Overdosage of morphine is characterized by respiratory depression, with or without concomitant CNS depression. In severe overdosage, apnea, circulatory collapse, cardiac arrest and death may occur. The conditions that might cause an overdosage situation may vary from patient to patient. A DepoDur dose that is within the labeled dosing guidelines may be found to be more than could be tolerated by an individual patient. During post-marketing experience, spontaneous cases of apnea, respiratory arrest, and cardiac arrest have been reported after administration of labeled DepoDur doses (see WARNINGS and ADVERSE EVENTS). Since respiratory arrest may result either through direct depression of the respiratory center or as the result of hypoxia, attention should primarily be given to the establishment of adequate respiratory exchange through provision of a patent airway and institution of assisted or controlled ventilation. Opiates administered in addition to DepoDur to manage pain may precipitate or worsen adverse events such as respiratory depression. Additional opiates should be administered with caution.

The opiate antagonist, naloxone, is a specific antidote. An initial dose of 0.4 to 2 mg of naloxone should be administered intravenously, simultaneously with respiratory resuscitation. If the desired degree of counteraction and improvement in respiratory function is not obtained, naloxone may be repeated at 2- to 3-minute intervals. If no response is observed after 10 mg of naloxone has been administered, the diagnosis of opiate-induced, or partial opiate-induced, toxicity should be questioned. Intramuscular or subcutaneous administration may be used if the intravenous route is not available.

As the duration of effect of naloxone is considerably shorter than that of DepoDur, repeated administration or continuous infusion of naloxone may be necessary. Patients should be closely observed for evidence of recurrence of respiratory depression.

DOSAGE AND ADMINISTRATION

DepoDur is intended only for lumbar epidural administration prior to surgery or after clamping of the umbilical cord during cesarean section. DepoDur may be administered via needle or catheter at the lumbar level. Administration of DepoDur at the thoracic level or higher is not recommended because it has not been studied. DepoDur may be administered undiluted or may be diluted up to 5 mL total volume with PRESERVATIVE-FREE 0.9% normal saline.

Vials of DepoDur should be gently inverted to re-suspend the particles immediately prior to withdrawal from the vial. Avoid aggressive agitation. No further reconstitution or dilution is required.

For major orthopedic surgery of the lower extremity the recommended dose of DepoDur is 15 mg. For lower abdominal or pelvic surgery, the recommended dose of DepoDur is 10-15 mg. Some patients may benefit from a 20-mg dose of DepoDur, but the incidence of serious adverse respiratory events was dose-related in clinical trials. For cesarean section, the recommended dose is 10 mg.

DepoDur should be administered to elderly patients (>65 years) after careful evaluation of their underlying medical condition and consideration of the risks associated with DepoDur. Vigilant perioperative monitoring should be exercised for elderly patients receiving DepoDur. In general, as with all opiates, the dose for elderly or debilitated patients should be at the low end of the dosing range.

While DepoDur is indicated for women undergoing cesarean section following clamping of the umbilical cord, DepoDur should not be administered to women for vaginal labor and delivery.

The safety and effectiveness of DepoDur in pediatric patients below the age of 18 years have not been established and use in this population is not recommended.

DepoDur should be administered by or under the direct supervision of a physician experienced in the technique of epidural administration and who is thoroughly familiar with the risks associated with the drug product. It should be administered only in settings where there is adequate patient monitoring. Resuscitative equipment and a specific antagonist (naloxone injection) should be immediately available for the management of respiratory depression. Patient monitoring should be continued for at least 48 hours after dosing, as delayed respiratory depression may occur (see WARNINGS).

Improper placement of a needle or catheter in the epidural space should be ruled out before DepoDur is injected. Techniques to detect improper placement of a needle or catheter include: a) aspiration to check for the presence of blood or cerebrospinal fluid and/or b) administration of a 3-mL test dose of 1.5% PRESERVATIVE-FREE lidocaine and epinephrine (1:200,000). If a test dose is administered, the patient should be observed for tachycardia or sudden onset of segmental anesthesia, indicating that intrathecal injection has occurred. To minimize a pharmacokinetic interaction of DepoDur with the test dose, flush the epidural catheter with 1 mL of PRESERVATIVE-FREE 0.9% normal saline and wait at least 15 minutes after administration of the test dose.

Do not mix DepoDur with any other medications. Once DepoDur has been administered, no other medication should be administered into the epidural space for at least 48 hours.

Do not use an in-line filter during administration of DepoDur.

Although DepoDur is a sterile agent, it does not contain any bacteriostatic agents. Therefore, DepoDur must be administered within 4 hours after withdrawal from the vial. Do not heat-sterilize or gas-sterilize.

Discard any unused portion in a manner appropriate for Schedule II substances.

PROTECT DEPODUR FROM FREEZING. DO NOT ADMINISTER DEPODUR IF IT IS SUSPECTED THAT THE VIAL HAS BEEN FROZEN.

SAFETY AND HANDLING INSTRUCTIONS

DepoDur consists of morphine encapsulated in multivesicular lipid-based particles that pose no known risk of handling to healthcare workers. Vials of DepoDur should be gently inverted to re-suspend the particles immediately prior to withdrawal from the vial.

Each vial of DepoDur contains a potent opiate that has been associated with abuse and dependence among health care providers. Appropriate measures should be taken to control this product within the hospital or clinic including rigid accounting, rigorous control of wastage, and restricted access.

Protect DepoDur from freezing. Do not administer DepoDur if it is suspected that the vial has been frozen. Each carton of DepoDur includes a freeze indicator that should be checked prior to administration of the product. Do not administer DepoDur, if the bulb of the freeze indicator has changed from clear to pink or purple, as this indicates that the product may have frozen. Freezing may adversely affect the modified release mechanism of DepoDur.

As a convenience to the hospital pharmacist, each carton of DepoDur includes pharmacy stickers for noting when each vial has been removed from refrigeration and advising to resuspend just prior to use. Following withdrawal from the vial DepoDur may be held at 15° to 30°C (59° to 86°F) for up to 4 hours prior to administration.

HOW SUPPLIED

Preservative-free DepoDur (morphine sulfate extended- release liposome injection) is available in 10 mg/mL single-use, amber vials for epidural administration.

10 mg/1 mL vial packaged in cartons of 5 (NDC 24477-020-04)
15 mg/1.5 mL vial packaged in cartons of 5 (NDC 24477-020-05)

STORAGE

Protect from freezing. DepoDur should be routinely stored in the refrigerator at 2° to 8°C (36° to 46°F). Keep DepoDur vials in carton during refrigeration. DepoDur may be held at controlled room temperature for up to 30 days in sealed, intact (unopened) vials. Vials stored at controlled room temperature may be separated from the carton, but should not be returned to a refrigerator. Discard vials that have been stored at room temperature for over 30 days

Manufactured for:
EKR Therapeutics, Inc.
Cedar Knolls NJ 07927

Manufactured by:
Pacira Pharmaceuticals
San Diego, CA 92121

Copyright © Pacia Pharmaceuticals Inc. 2007

Printed in U.S.A December, 2007
2007-02